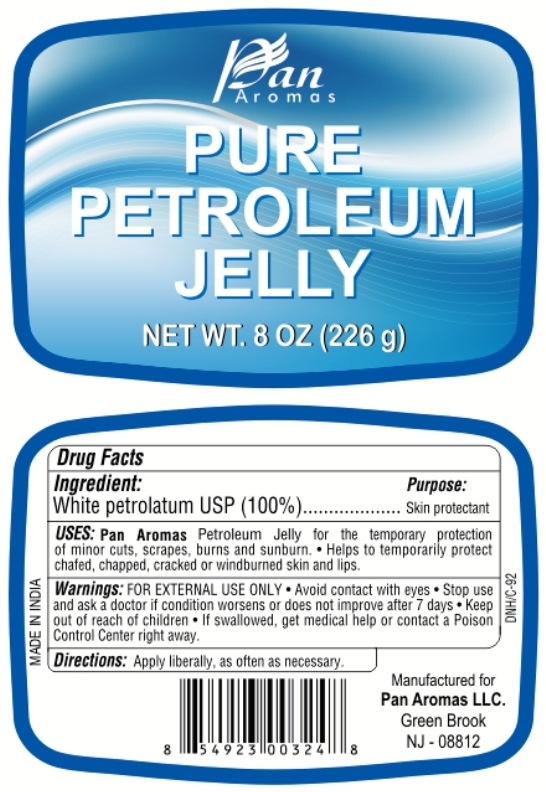 DRUG LABEL: Pure Petroleum
NDC: 50346-001 | Form: JELLY
Manufacturer: Pan Aromas LLC
Category: otc | Type: HUMAN OTC DRUG LABEL
Date: 20120526

ACTIVE INGREDIENTS: PETROLATUM 1 g/1 g

PURE PETROLEUM JELLY

Active ingredient

White petrolatum USP (100 %)

Purpose

Skin protectant

Uses

- For the temporary protection of minor cuts, scraps, burns and sunburn.
- Helps to temporarily protect chafed, chapped, cracked or windburned skin and lips.

Warnings

For external use only.

Do not use

over deep or puncture wounds, infections or lacerations. Ask a doctor.

When using this product

avoid contact with eyes.

Stop use and ask a doctor

if condition worsens or does not improve after 7 days.

Keep out of reach of children

If swallowed get medical help or contact a Poison Control Center right away.

Directions

Apply liberally, as often as necessary.

Inactive ingredients

None

PRINCIPAL DISPLAY PANEL

PURE PETROLEUM JELLY
NET WT. 8 OZ (226 g)